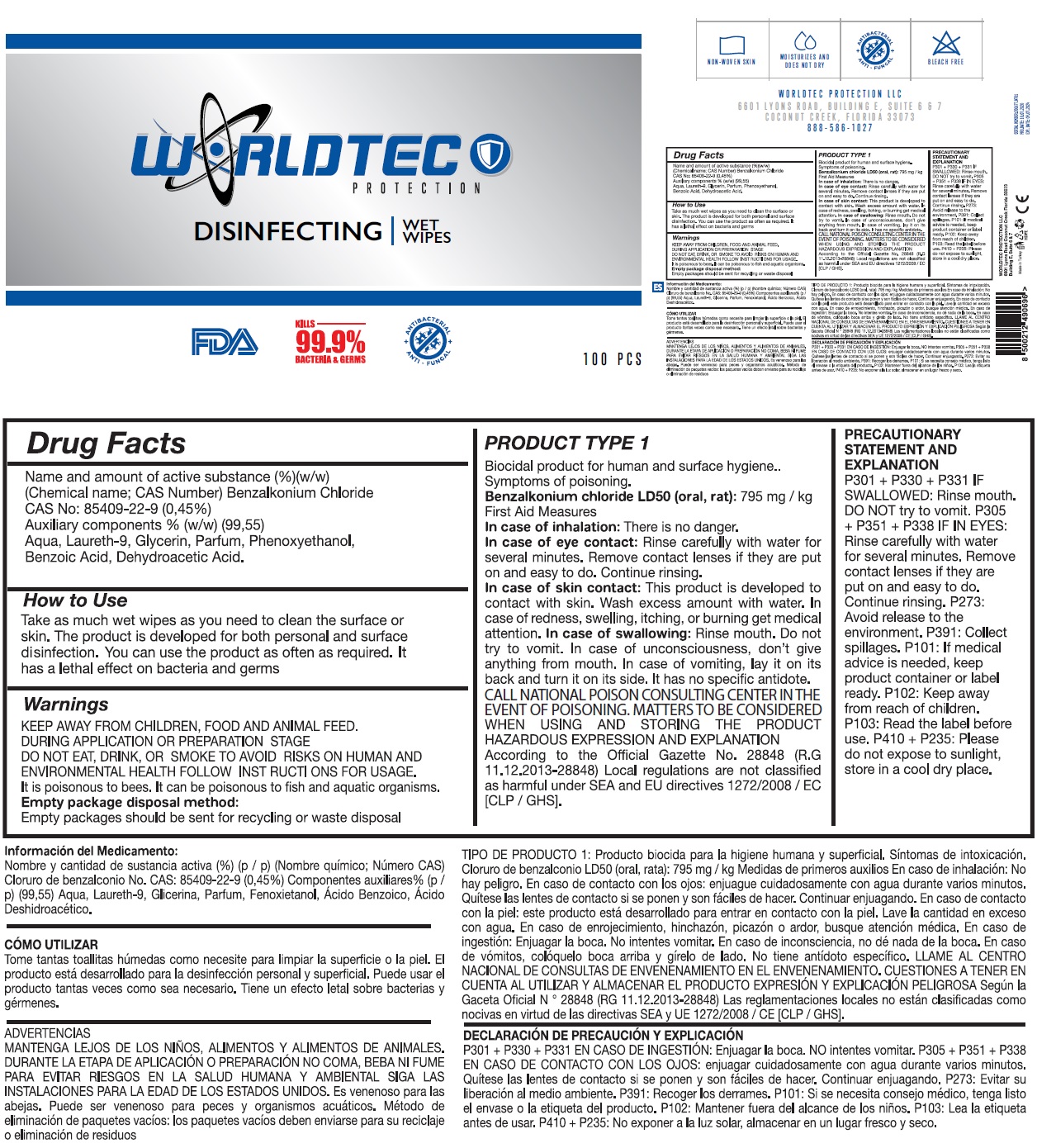 DRUG LABEL: WORLDTEC DISINFECTING WET WIPES
NDC: 76725-008 | Form: CLOTH
Manufacturer: MAKYAJ KOZMETIK INSAAT SANAYI VE TICARET LIMITED SIRKETI
Category: otc | Type: HUMAN OTC DRUG LABEL
Date: 20200829

ACTIVE INGREDIENTS: BENZALKONIUM CHLORIDE 0.45 g/100 g
INACTIVE INGREDIENTS: WATER; POLIDOCANOL; GLYCERIN; PHENOXYETHANOL; BENZOIC ACID; DEHYDROACETIC ACID

WORLDTEC PROTECTION DISINFECTING WET WIPES

Name and amount of active substance (%)(w/w)

(Chemical name; CAS Number) Benzalkonium Chloride

CAS No: 85409-22-9 (0,45%)

Auxiliary components % (w/w) (99,55)

Aqua, Laureth-9, Glycerin, Parfum, Phenoxyethanol, Benzoic Acid, Dehydroacetic Acid.

Purpose

ANTIBACTERIAL

ANTI-FUNGAL

INDICATIONS AND USAGE

Use The product is developed for both personal and surface disinfection. It has a lethal effect on bacteria and germs

Warnings

DURING APPLICATION OR PREPARATION STAGE DO NOT EAT, DRINK, OR SMOKE TO AVOID RISKS

ON HUMAN AND ENVIRONMENTAL HEALTH FOLLOW INSTRUCTIONS FOR USAGE.

It is poisonous to bees. It can be poisonous to fish and aquatic organisms.

PRODUCT TYPE 1

Biocidal product for human and surface hygiene..

Symptoms of poisoning

Benzalkonium chloride LD50 (oral, rat): 795 mg / kg

First Aid Measures

In case of inhalation: There is no danger.

In case of eye contact: Rinse carefully with water for several minutes. Remove contact lenses if they are put on and easy to do. Continue rinsing

In case skin contact: This product is developed to contact with skin. Wash excess amount with water. In case of redness, swelling, itching, or burning get medical attention. In case of swallowing: Rinse mouth. Do not try to vomit. In case of unconsciousness, don't give anything from mouth. In case of vomiting, lay it on its back and turn it on its side. It has no specific antidote.

CALL NATIONAL POISON CONSULTING CENTER IN THE EVENT OF POISONING. MATTERS TO BE CONSIDERED WHEN USING AND STORING THE PRODUCT HAZARDOUS EXPRESSION AND EXPLANATION.

According to the Official Gazette No. 28848 (R.G. 11. 12.2013-28848) Local regulations are not classified as harmful under SEA and EU directives 1272/2008 / EC [CLP / GHS].

PRECAUTIONARY STATEMENT AND EXPLANATION

P301 + P330 + P331 IF SWALLOWED: Rinse mouth. DO NOT try to vomit. P305 + P351 + P338 IF IN EYES: Rinse carefully with water for several minutes. Remove contact lenses if they are put on and easy to do. Continue rinsing.

KEEP AWAY FROM CHILDREN, FOOD AND ANIMAL FEED.

How to Use

Take as much wet wipes as you need to clean the surface or skin. You can use the product as often as required.

Other Information

Empty package disposal method:

Empty package should be sent for recycling or waste disposal

P273: Avoid release to the environment. P391: Collect spillages. P101: If medical advice is needed,

keep product container or label ready. P102: Keep away from reach of children. P103: Read the label

before use. P410 + P235: Please do not expose to sunlight, store in a cool dry place.

FDA

KILLS 99.9% BACTERIA & GERMS

NON-WOVEN SKIN

MOISTURIZES AND DOES NOT DRY

BLEACH FREE

WORLDTEC PROTECTION LLC

6601 LYONS ROAD, BUILDING E, SUITE 6 & 7,

COCONUT CREEK, FLORIDA 33073

888-586-1027

Made in Turkey